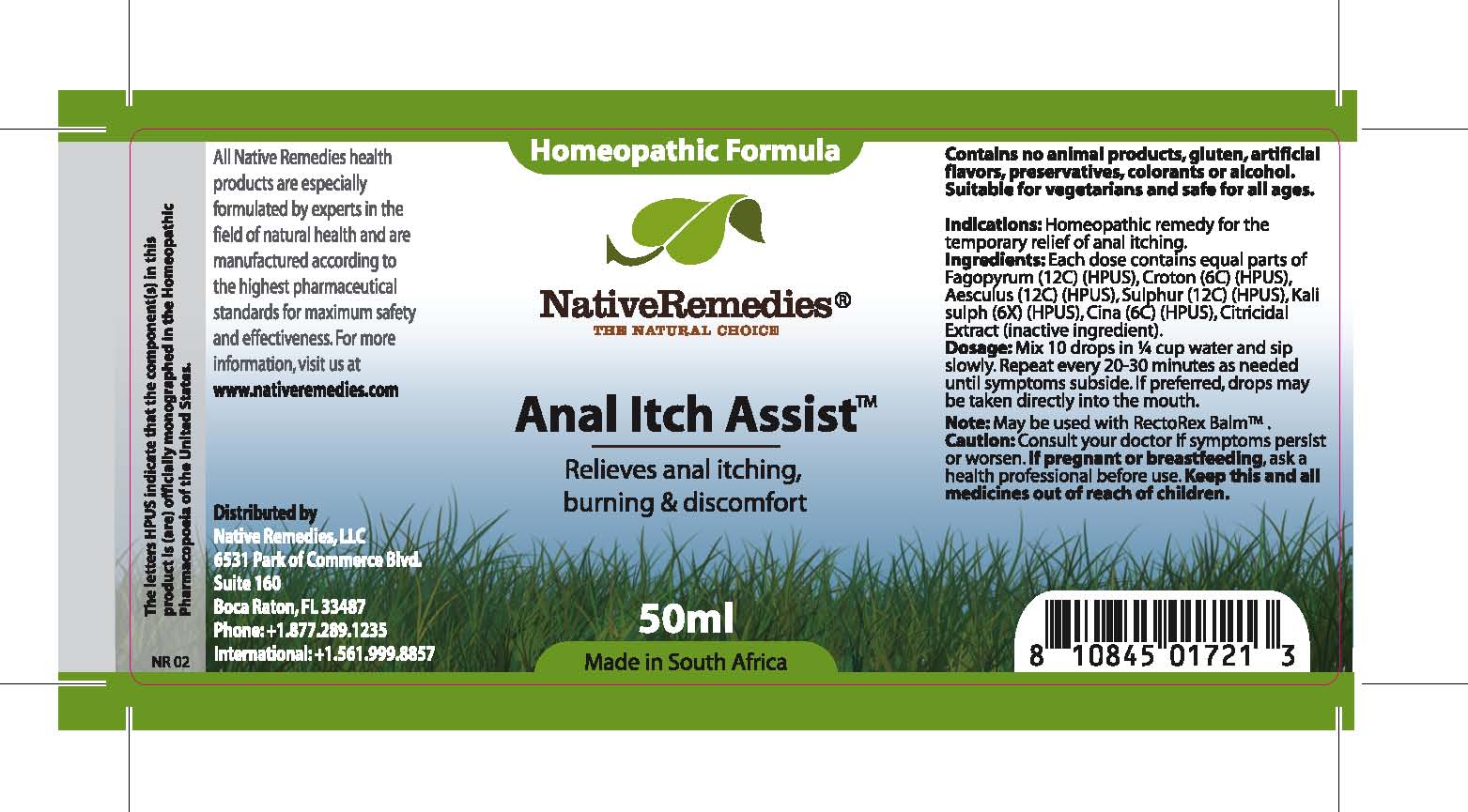 DRUG LABEL: Anal Itch Ease
NDC: 68647-169 | Form: TINCTURE
Manufacturer: Feelgood Health
Category: homeopathic | Type: HUMAN OTC DRUG LABEL
Date: 20100921

ACTIVE INGREDIENTS: BUCKWHEAT 12 [hp_C]/33.3 mL; CASTOR OIL 6 [hp_C]/33.3 mL; AESCULUS CARNEA FLOWER 12 [hp_C]/33.3 mL; SULFUR 12 [hp_C]/33.3 mL; POTASSIUM SULFATE 6 [hp_X]/33.3 mL; ARTEMISIA CINA FLOWER 6 [hp_C]/33.3 mL
INACTIVE INGREDIENTS: CITRUS PARADISI SEED 0.125 mL/50 mL; WATER 49.486 mL/50 mL

ANAL ITCH ASSIST

PURPOSE

Relieves anal itching, burning and discomfort

INDICATIONS AND USAGE

Indications: Homeopathic remedy for the relief of anal itching.

DOSAGE AND ADMINISTRATION

Dosage: Mix 10 drops in ¼ cup water and sip slowly. Repeat every 20-30 minutes as needed until symptoms subside. If preferred, drops may be taken directly into the mouth. May be used with RectoRex Balm™ .

GENERAL PRECAUTIONS

Caution: Consult your doctor if symptoms persist or worsen. Keep this and all medicines out of reach of children.

ACTIVE INGREDIENT

Ingredients: Each dose contains equal parts of Fagopyrum (12C) (HPUS), Croton (6C) (HPUS), Aesculus (12C) (HPUS), Sulphur (12C) (HPUS), Kali sulph (6X) (HPUS), Cina (6C) (HPUS)

Citricidal Extract (inactive ingredient).

PREGNANCY

If pregnant or breastfeeding, ask a health professional before use.

WARNINGS

Contains no animal products, gluten, artificial flavors, preservatives, colorants or alcohol. Suitable for vegetarians and safe for all ages.

PATIENT COUNSELING INFORMATION

All Native Remedies health products are especially formulated by experts in the field of natural health and are manufactured according to the highest pharmaceutical standards for maximum safety and effectiveness. For more information, visit us at www.nativeremedies.com

Distributed by

Native Remedies, LLC

6531 Park of Commerce Blvd.

Suite 160

Boca Raton, FL 33487

Phone: +1.877.289.1235

International: +1.561.999.8857

The letters HPUS indicate that the component(s) in this product is (are) officially monographed in the Homeopathic Pharmacopoeia of the United States.

KEEP OUT OF REACH OF CHILDREN

Keep this and all medicines out of reach of children.